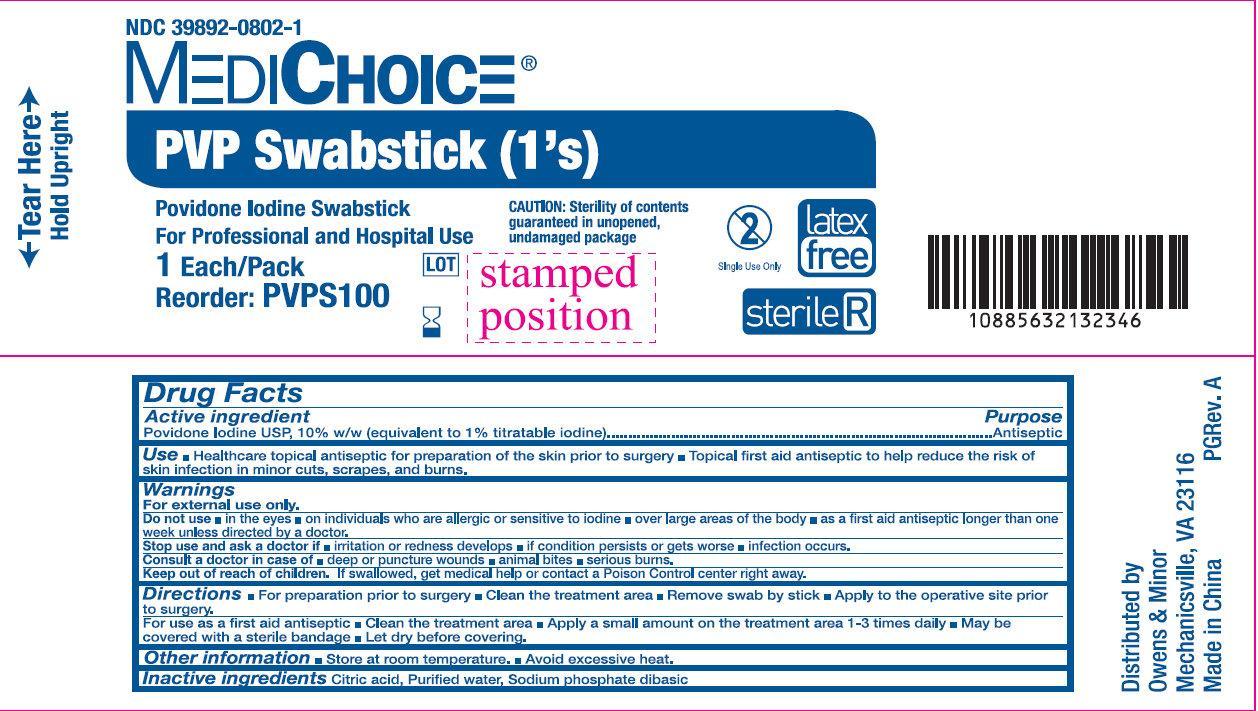 DRUG LABEL: MediChoice PVP Swabsticks
NDC: 39892-0802 | Form: SWAB
Manufacturer: O&M HALYARD, INC.
Category: otc | Type: HUMAN OTC DRUG LABEL
Date: 20251008

ACTIVE INGREDIENTS: POVIDONE-IODINE 10 g/100 g
INACTIVE INGREDIENTS: CITRIC ACID ACETATE; WATER; SODIUM PHOSPHATE, DIBASIC

MediChoice PVP Swabsticks (1's)

Active ingredient

Povidone Iodine 10% (equivalent to 1% titratable iodine)

Purpose

Antiseptic

Use

- Healthcare topical antiseptic for preparation of the skin prior to surgery
- Topical first aid antiseptic to help reduce the risk of skin infection in minor cuts, scrapes and burns.

Warnings

For external use only.

Do not use

- in the eyes
- on individuals who are allergic or sensitive to iodine
- over large areas of the body
- as a first aid antiseptic longer than one week unless directed by a doctor.

Stop use and ask a doctor

- if irritation and redness develop
- if condition persists or gets worse
- infection occurs

- deep or puncture wounds
- animal bites
- serious burns.

Consult a doctor in case of

Keep out of reach of children.

If swallowed, get medical help or contact a Poison Control Center right away.

Directions

For preparation of the skin prior to surgery

For use as a first aid antiseptic

- Clean the treatment area
- Remove swab by the stick
- Apply to the operative site prior to surgery.

- Clean the treatment area
- Apply a small amount on the treatment area 1-3 times daily
- May be covered with a sterile bandage
- Let dry before covering.

Other information

- Store at room temperature
- Avoid excessive heat.

Inactive ingredients

Citric Acid, Purified water, Sodium phosphate dibasic